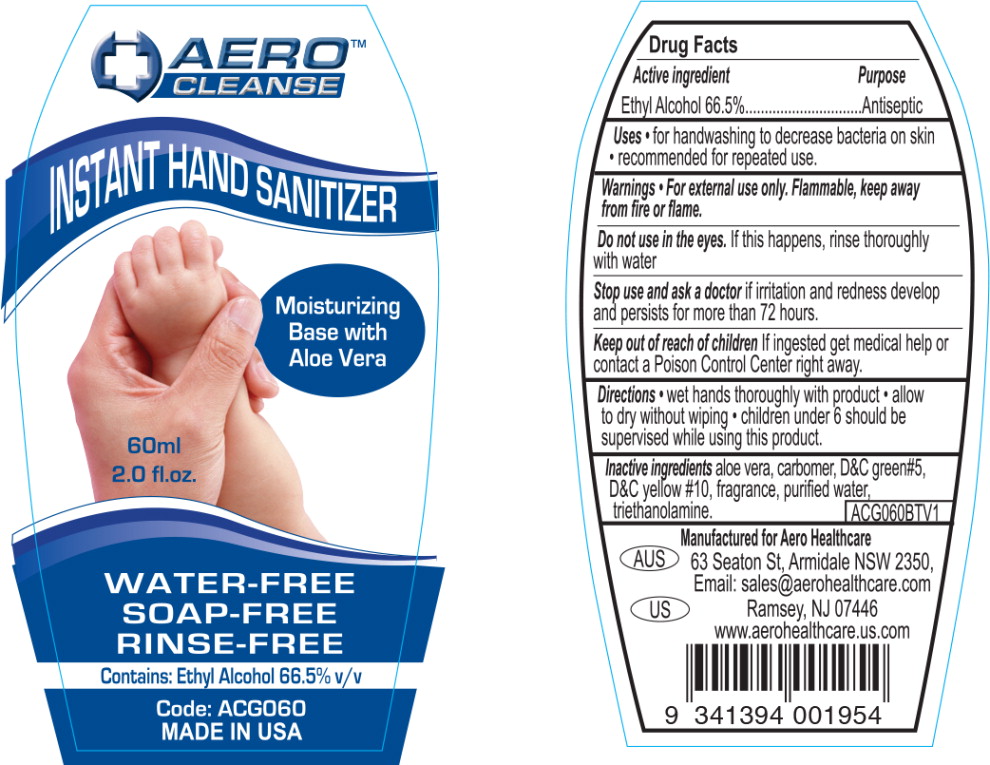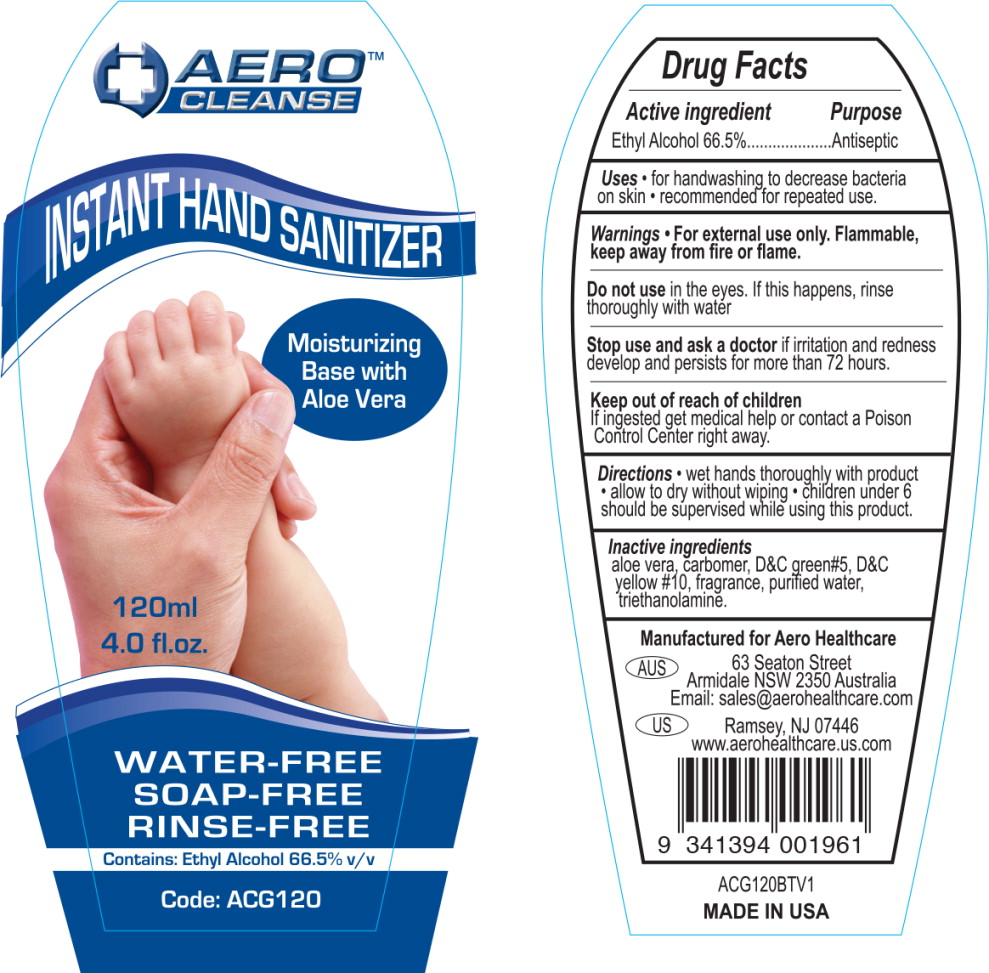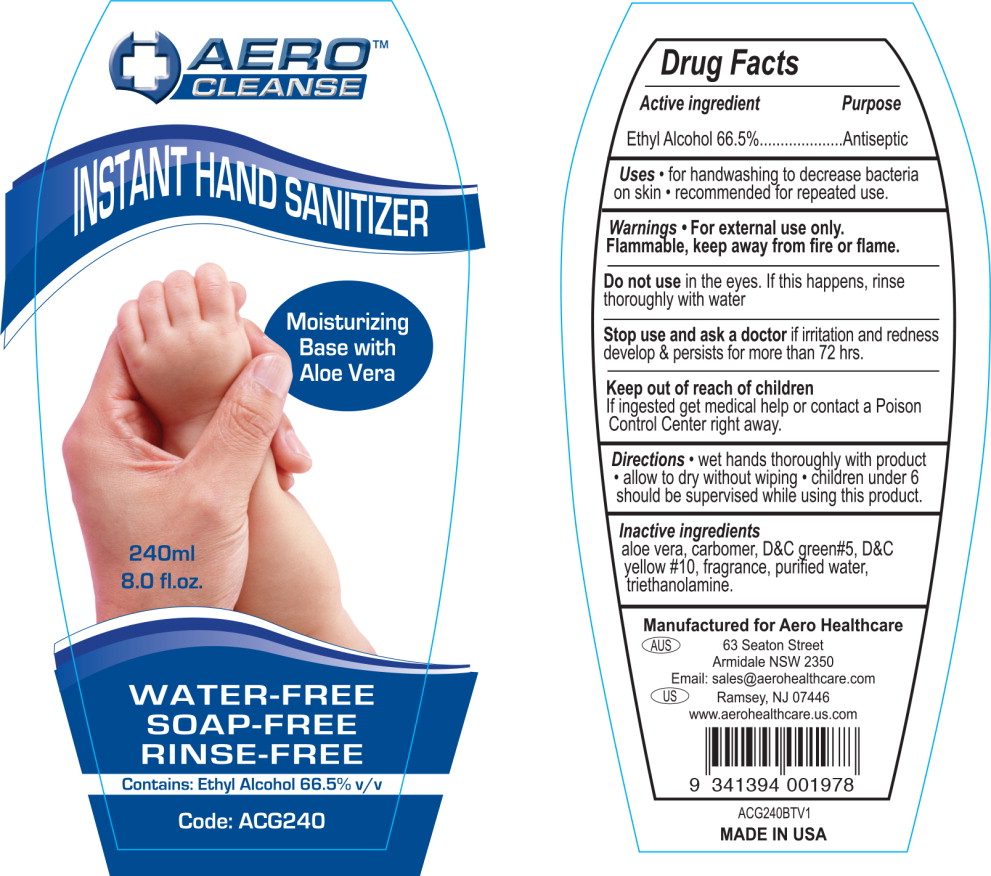 DRUG LABEL: Instant Hand Sanitizer
NDC: 55305-111 | Form: GEL
Manufacturer: Aero Healthcare
Category: otc | Type: HUMAN OTC DRUG LABEL
Date: 20131230

ACTIVE INGREDIENTS: alcohol 0.665 g/1 mL
INACTIVE INGREDIENTS: aloe vera leaf; carbomer interpolymer type a (55000 mpa.s); d&c green no. 5; d&c yellow no. 10; water; trolamine

INSTANT HAND SANITIZER

Aero Healthcare

Drug Facts

Active Ingredients

Ethyl Alcohol 66.5%

Purpose

Antiseptic

Uses

- for handwashing to decrease bacteria on skin
- recommended for repeated use

Warnings

For external use only. Flammable, keep away from fire or flame.

Do not use in the eyes. If this happens, rinse thoroughly with water

Stop use and ask doctor if irritation and redness develop and persists for more than 72 hours.

Keep out of reach of children If ingested get medical help or contact a Poison Control Center right away.

Directions

- wet hands thoroughly with product
- allow to dry without wiping
- children under 6 should be supervised while using this product

Inactive ingredients

Aloe vera, carbomer, D&C green#5, D&C yellow #10, fragrance, purified water, triethanolamine

Manufactured for Aero Healthcare
63 Seaton St, Armidale, NSW 2350,
Email: sales@aerohealthcare.com
Ramsey, NJ 07446
www.aerohealthcare.us.com

PRINCIPAL DISPLAY PANEL – 2 fl. oz. Bottle Label

AERO
CLEANSE

INSTANT HAND SANITIZER

Moisturizing
Base with

Aloe Vera

60ml

2.0 fl.oz.

WATER-FREE

SOAP-FREE

RINSE-FREE

Contains: Ethyl Alcohol 66.5% v/v

Code: ACG060

MADE IN USA

PRINCIPAL DISPLAY PANEL – 4 fl. oz. Bottle Label

AERO
CLEANSE

INSTANT HAND SANITIZER

Moisturizing
Base with

Aloe Vera

120ml

4.0 fl.oz.

WATER-FREE

SOAP-FREE

RINSE-FREE

Contains: Ethyl Alcohol 66.5% v/v

Code: ACG120

PRINCIPAL DISPLAY PANEL – 8 fl. oz. Bottle Label

AERO
CLEANSE

INSTANT HAND SANITIZER

Moisturizing
Base with

Aloe Vera

240ml

8.0 fl.oz.

WATER-FREE

SOAP-FREE

RINSE-FREE

Contains: Ethyl Alcohol 66.5% v/v

Code: ACG240